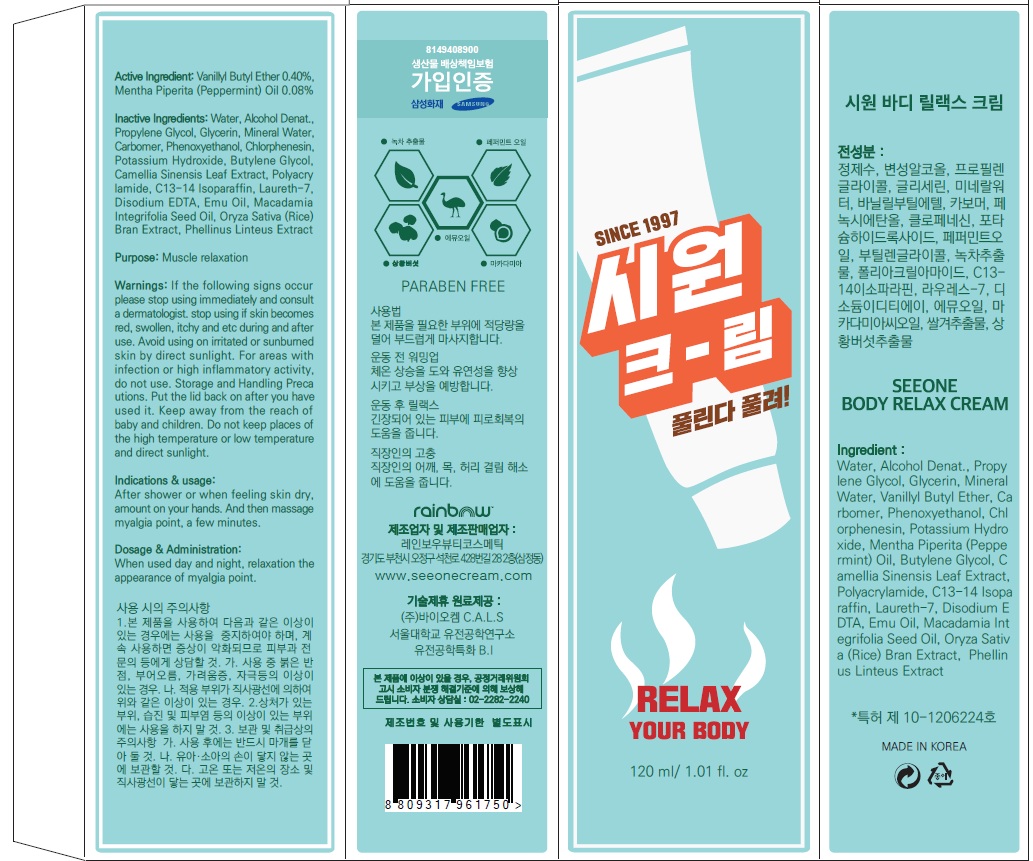 DRUG LABEL: SEEONE BODY RELAX
NDC: 71193-010 | Form: CREAM
Manufacturer: Rainbow Beauty Cosmetic
Category: otc | Type: HUMAN OTC DRUG LABEL
Date: 20170120

ACTIVE INGREDIENTS: VANILLYL BUTYL ETHER 0.48 g/120 mL; PEPPERMINT OIL 0.09 g/120 mL
INACTIVE INGREDIENTS: Water; Propylene Glycol

ACTIVE INGREDIENT

Active Ingredient: Vanillyl Butyl Ether 0.40%, Mentha Piperita (Peppermint) Oil 0.08%

INACTIVE INGREDIENT

Inactive Ingredients: Water, Alcohol Denat., Propylene Glycol, Glycerin, Mineral Water, Carbomer, Phenoxyethanol, Chlorphenesin, Potassium Hydroxide, Butylene Glycol, Camellia Sinensis Leaf Extract, Polyacrylamide, C13-14 Isoparaffin, Laureth-7, Disodium EDTA, Emu Oil, Macadamia Integrifolia Seed Oil, Oryza Sativa (Rice) Bran Extract, Phellinus Linteus Extract

PURPOSE

Purpose: Muscle relaxation

WARNINGS

Warnings: If the following signs occur please stop using immediately and consult a dermatologist. stop using if skin becomes red, swollen, itchy and etc during and after use. Avoid using on irritated or sunburned skin by direct sunlight. For areas with infection or high inflammatory activity, do not use. Storage and Handling Precautions. Put the lid back on after you have used it. Keep away from the reach of baby and children. Do not keep places of the high temperature or low temperature and direct sunlight.

KEEP OUT OF REACH OF CHILDREN

INDICATIONS & USAGE

Indications & usage: After shower or when feeling skin dry, amount on your hands. And then massage myalgia point, a few minutes.

DOSAGE & ADMINISTRATION

Dosage & Administration: When used day and night, relaxation the appearance of myalgia point.